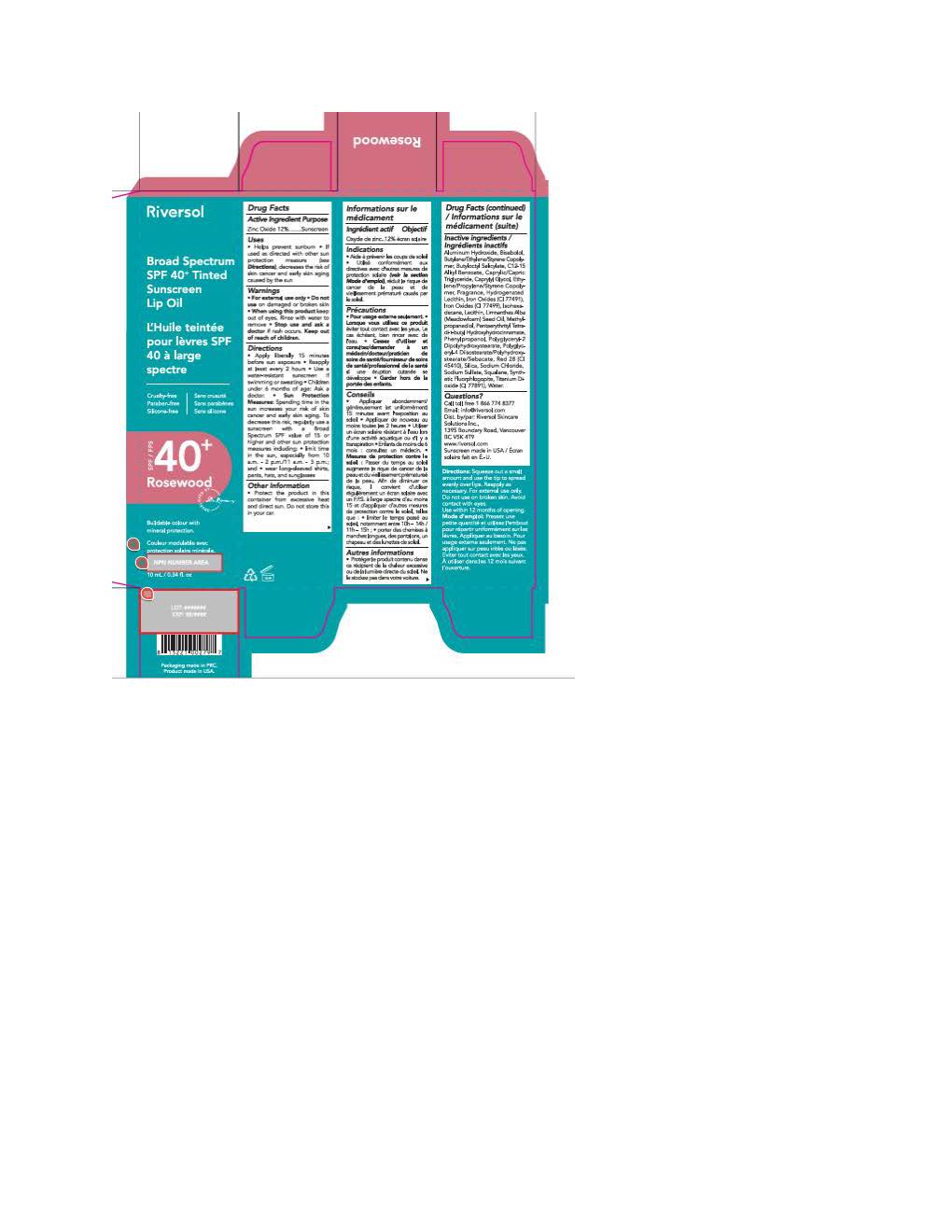 DRUG LABEL: Riversol Tinted Lip Oil
NDC: 72019-2120 | Form: LOTION
Manufacturer: Riversol Skincare
Category: otc | Type: HUMAN OTC DRUG LABEL
Date: 20251117

ACTIVE INGREDIENTS: ZINC OXIDE 110 mg/1 mL
INACTIVE INGREDIENTS: ALKYL (C12-15) BENZOATE; CAPRYLIC/CAPRIC TRIGLYCERIDE; CAPRYLYL GLYCOL; POLYGLYCERYL-4 DIISOSTEARATE/POLYHYDROXYSTEARATE/SEBACATE; WATER; CALCIUM SULFATE; ROSIN; PENTAERYTHRITYL TETRA-DI-T-BUTYL HYDROXYHYDROCINNAMATE; SODIUM SULFATE; .ALPHA.-BISABOLOL, (+)-; SILICON DIOXIDE; RED 7; LECITHIN, SOYBEAN; SODIUM CHLORIDE; FERROSOFERRIC OXIDE; PHENYLPROPANOL; FERRIC OXIDE RED; METHYLPROPANEDIOL; ISOHEXADECANE; LIMNANTHES ALBA (MEADOWFOAM) SEED OIL; BUTYLOCTYL SALICYLATE; ALUMINUM HYDROXIDE; POLYGLYCERYL-2 DIPOLYHYDROXYSTEARATE; SQUALANE; DISPERSE BLUE 1; FERRIC OXIDE YELLOW

Riversol Tinted Lip Oil